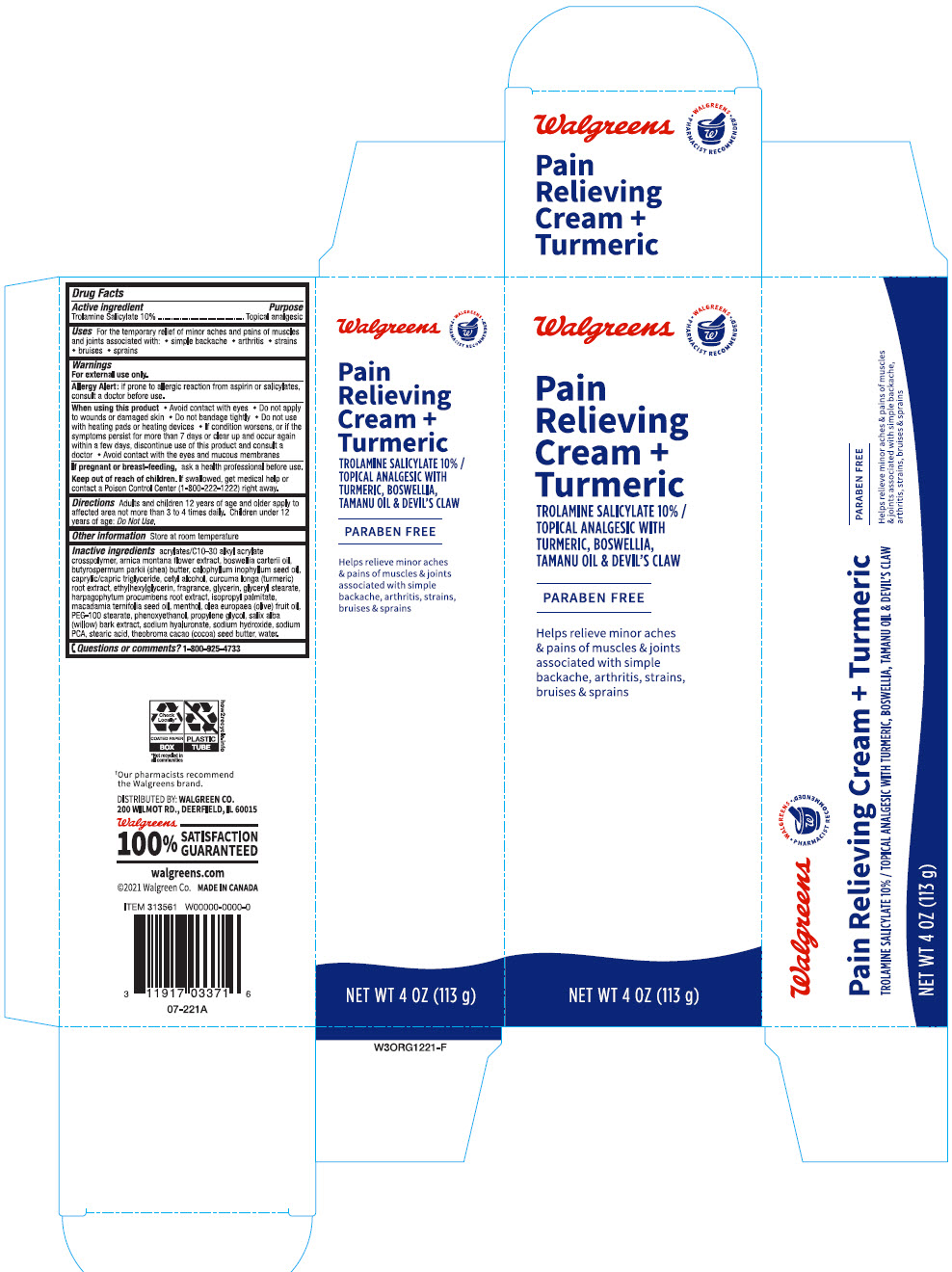 DRUG LABEL: Walgreens Pain Relieving Plus Turmeric
NDC: 0363-3630 | Form: CREAM
Manufacturer: Walgreen Company
Category: otc | Type: HUMAN OTC DRUG LABEL
Date: 20241031

ACTIVE INGREDIENTS: Trolamine Salicylate 100 mg/1 g
INACTIVE INGREDIENTS: CARBOMER INTERPOLYMER TYPE A (ALLYL SUCROSE CROSSLINKED); ARNICA MONTANA FLOWER; FRANKINCENSE OIL; SHEA BUTTER; TAMANU OIL; MEDIUM-CHAIN TRIGLYCERIDES; Cetyl Alcohol; TURMERIC; Ethylhexylglycerin; Glycerin; GLYCERYL MONOSTEARATE; HARPAGOPHYTUM PROCUMBENS ROOT; Isopropyl Palmitate; MACADAMIA OIL; MENTHOL, UNSPECIFIED FORM; OLIVE OIL; PEG-100 Stearate; Phenoxyethanol; Propylene Glycol; SALIX ALBA BARK; HYALURONATE SODIUM; Sodium Hydroxide; SODIUM PYRROLIDONE CARBOXYLATE; Stearic Acid; COCOA BUTTER; Water

Walgreens Pain Relieving Cream + Turmeric
Topical Analgesic

Drug Facts

Active ingredient

Trolamine Salicylate 10%

Purpose

Topical analgesic

Uses

For the temporarily relief of minor aches and pains of muscles and joint associated with:

- simple backache
- arthritis
- strains
- bruises
- sprains

Warnings

For external use only

Allergy Alert: if prone to allergic reaction from aspirin or salicylates, consult a doctor before use.

When using this product

- Avoid contact with eyes
- Do not apply to wounds or damaged skin
- Do not bandage tightly
- Do not use with heating pads or heating devices
- If condition worsens, or if the symptoms persist for more than 7 days or clear up and occur again within a few days, discontinue use of this product and consult a doctor
- Avoid contact with the eyes and mucous membranes

PREGNANCY OR BREAST FEEDING

If pregnant or breast-feeding, ask a health professional before use.

Keep out of reach of children. If swallowed, get medical help or contact a Poison Control Center (1-800-222-1222) right away.

Directions

Adults and children 12 years of age and older apply to affected area not more than 3 to 4 times daily. Children under 12 years of age: Do Not Use.

Other information

Store at room temperature

Inactive ingredients

acrylates/C10-30 alkyl acrylate crosspolymer, arnica montana flower extract, boswellia carterii oil, butyrospermum parkii (shea) butter, calophyllum inophyllum seed oil, caprylic/capric triglyceride, cetyl alcohol, curcuma longa (turmeric) root extract, ethylhexylglycerin, fragrance, glycerin, glyceryl stearate, harpagophytum procumbens root extract, isopropyl palmitate, macadamia ternifolia seed oil, menthol, olea europaea (olive) fruit oil, PEG-100 stearate, phenoxyethanol, propylene glycol, salix alba (willow) bark extract, sodium hyaluronate, sodium hydroxide, sodium PCA, stearic acid, theobroma cacao (cocoa) seed butter, water.

Questions or comments?

1-800-925-4733

DISTRIBUTED BY: WALGREEN CO.
200 WILMOT RD., DEERFIELD, IL 60015

PRINCIPAL DISPLAY PANEL - 113 g Tube Carton

Walgreens
• WALGREENS •
PHARMACIST RECOMMENDED†

Pain
Relieving
Cream +
Turmeric

TROLAMINE SALICYLATE 10% /
TOPICAL ANALGESIC WITH
TURMERIC, BOSWELLIA,
TAMANU OIL & DEVIL'S CLAW

PARABEN FREE

Helps relieve minor aches
& pains of muscles & joints
associated with simple
backache, arthritis, strains,
bruises & sprains

NET WT 4 OZ (113 g)